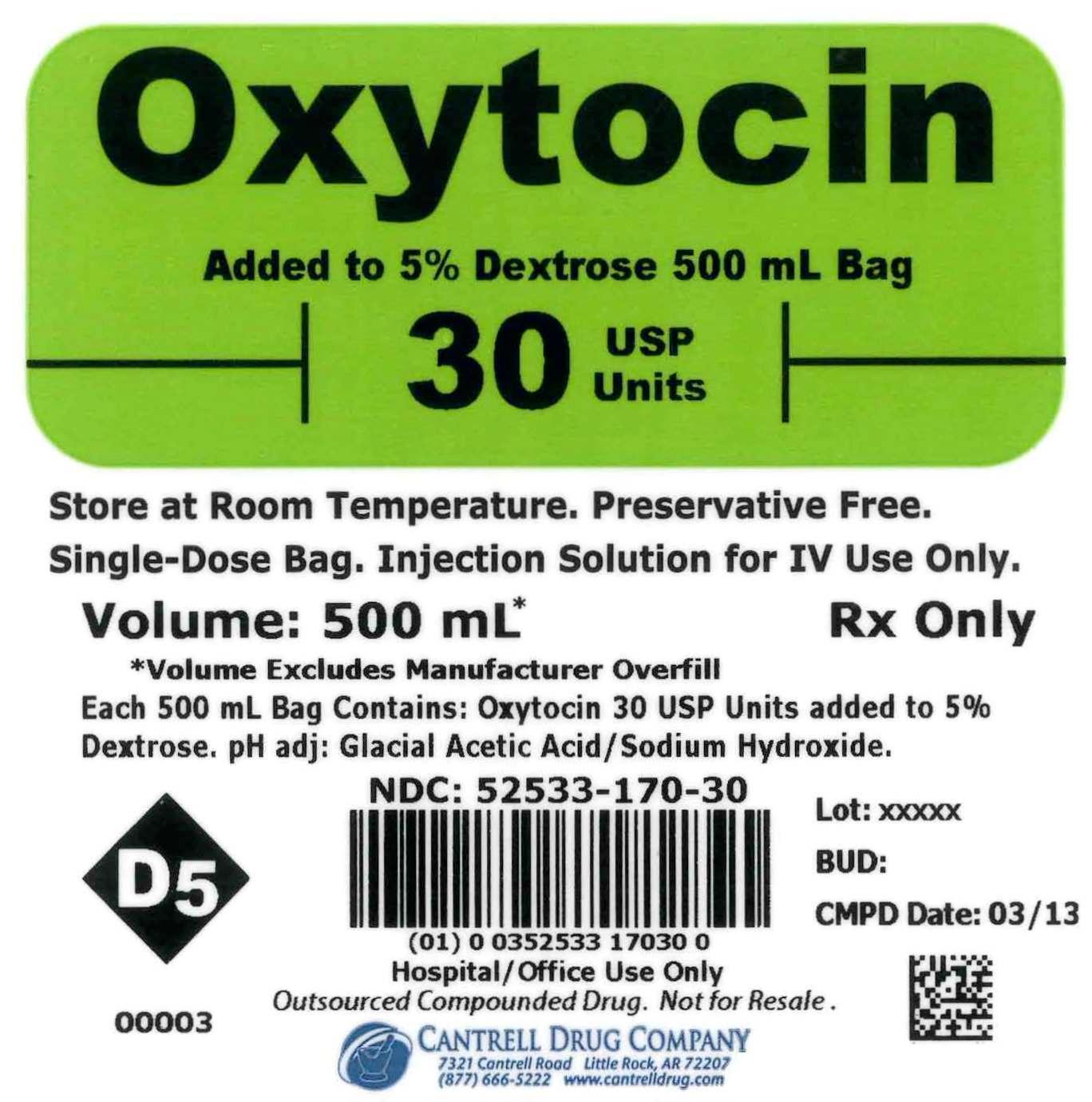 DRUG LABEL: Oxytocin
NDC: 52533-170 | Form: INJECTION, SOLUTION
Manufacturer: Cantrell Drug Company
Category: prescription | Type: HUMAN PRESCRIPTION DRUG LABEL
Date: 20141211

ACTIVE INGREDIENTS: OXYTOCIN 30 [USP'U]/500 mL
INACTIVE INGREDIENTS: DEXTROSE 25 g/500 mL; WATER

Oxytocin 30 USP Units Added to 5% Dextrose 500 mL Bag